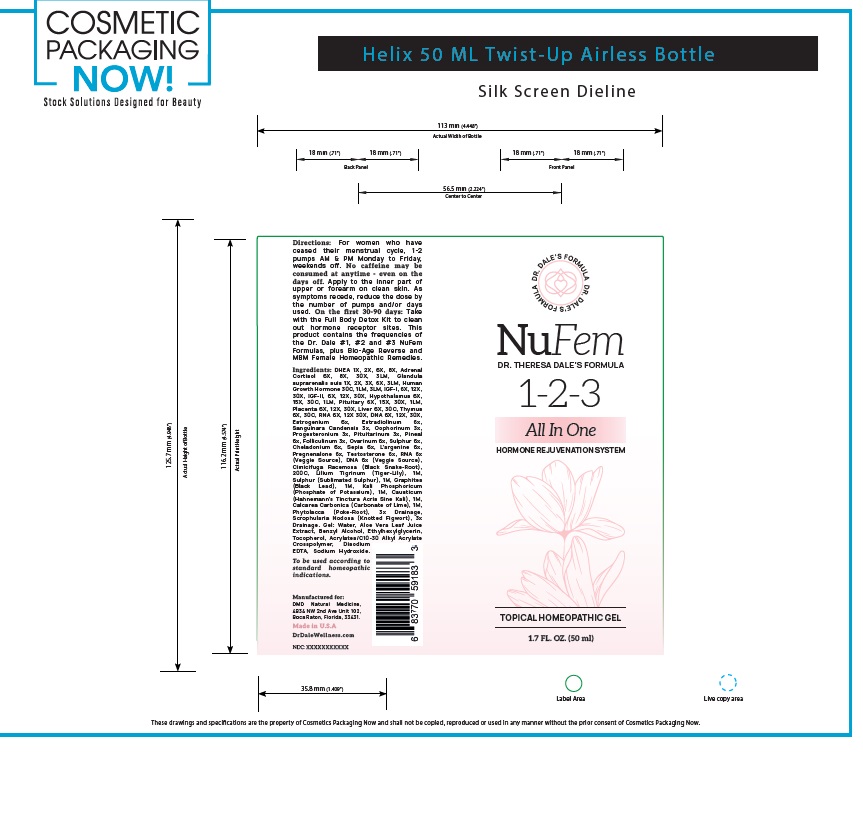 DRUG LABEL: Dr Dale Wellness  NU Fem 1 2 3 All In One Topical Homeopathic
NDC: 83230-001 | Form: GEL
Manufacturer: DMD Clinical Naturopathy
Category: homeopathic | Type: HUMAN OTC DRUG LABEL
Date: 20240321
DEA Schedule: CIII

ACTIVE INGREDIENTS: PRASTERONE 1 [hp_X]/50 mL; HYDROCORTISONE 6 [hp_X]/50 mL; SUS SCROFA ADRENAL GLAND 1 [hp_X]/50 mL; SOMATROPIN 1 [hp_M]/50 mL; INSULIN-LIKE GROWTH FACTOR 1 RECEPTOR 6 [hp_X]/50 mL; INSULIN-LIKE GROWTH FACTOR-2 6 [hp_X]/50 mL; BOS TAURUS HYPOTHALAMUS 6 [hp_X]/50 mL; HUMAN PLACENTAL TISSUE 6 [hp_X]/50 mL; BEEF LIVER 6 [hp_X]/50 mL; BOS TAURUS THYMUS 6 [hp_X]/50 mL; RNA-BINDING PROTEIN 10 6 [hp_X]/50 mL; APRINOCARSEN 6 [hp_X]/50 mL; ESTROGENS, ESTERIFIED 6 [hp_X]/50 mL; ESTRADIOL 6 [hp_X]/50 mL; SANGUINARIA CANADENSIS ROOT 3 [hp_X]/50 mL; SUS SCROFA OVARY 3 [hp_X]/50 mL; PROGESTERONE 3 [hp_X]/50 mL; BOS TAURUS PITUITARY GLAND, POSTERIOR 1 [hp_M]/50 mL; BOS TAURUS PINEAL GLAND 6 [hp_X]/50 mL; ESTRONE 3 [hp_X]/50 mL; BOS TAURUS OVARY 6 [hp_X]/50 mL; SULFUR 6 [hp_X]/50 mL; SEPIA OFFICINALIS JUICE 6 [hp_X]/50 mL; ARGININE 6 [hp_X]/50 mL; BLACK COHOSH 200 [hp_C]/50 mL; LILIUM LANCIFOLIUM WHOLE FLOWERING 1 [hp_M]/50 mL; GRAPHITE 1 [hp_M]/50 mL; POTASSIUM PHOSPHATE, UNSPECIFIED FORM 1 [hp_M]/50 mL; CAUSTICUM 1 [hp_M]/50 mL; OYSTER SHELL CALCIUM CARBONATE, CRUDE 1 [hp_M]/50 mL; PHYTOLACCA AMERICANA ROOT 3 [hp_X]/50 mL; SCROPHULARIA NODOSA WHOLE 3 [hp_X]/50 mL; TESTOSTERONE 6 [hp_X]/50 mL
INACTIVE INGREDIENTS: WATER; ALOE VERA LEAF; BENZYL ALCOHOL; ETHYLHEXYLGLYCERIN; TOCOPHEROL; ACRYLATES/C10-30 ALKYL ACRYLATE CROSSPOLYMER (60000 MPA.S); EDETATE DISODIUM; SODIUM HYDROXIDE; CHELIDONIUM MAJUS WHOLE

Active Ingredient (s)

DHEA 1X, 2X, 6X, 8X
Adrenal Cortisol 6X, 8X, 30X, 3LM
Glandula suprarenalis suis 1X, 2X, 3X, 6X, 3LM
Human Growth Hormone 30C, 1LM, 3LM, IGF-I, 6X, 12X, 30X, IGF-II, 6X, 12X, 30X
Hypothalamus 6X, 15X, 30C, 1LM
Pituitary 6X, 15X, 30X, 1LM
Placenta 6X, 12X, 30X
Liver 6X, 30C
Thymus 6X, 30C
RNA 6X, 12X 30X
DNA 6X, 12X, 30X.
Estrogenium 6x
Estradiolinum 6x
Sanguinara Candensis 3x
Oophorinum 3x
Progesteronium 3x
Pituitarinum 3x
Pineal 6x
Folliculinum 3x
Ovarinum 6x
Sulphur 6x
Cheladonium 6x

Sepia 6x
L’argenine 6x
Pregnenalone 6x
Testosterone 6x
RNA 6x (veggie source)
DNA 6x (veggie source)
Cimicifuga Racemosa (Black Snake-root), 200C
Lilium Tigrinum (Tiger-lily), 1M
Sulphur (Sublimated Sulphur), 1M
Graphites (Black Lead), 1M
Kali Phosphoricum (Phosphate of Potassium), 1M
Causticum (Hahnemann's tinctura acris sine Kali), 1M
Calcarea Carbonica (Carbonate of Lime), 1M
Phytolacca (Poke-root), 3x Drainage
Scrophularia Nodosa (Knotted Figwort), 3x Drainage

Purpose

For uncomfortable symptoms associated with menstrual cycle stopping due to age.

Uses

Topical gel, applied to skin

Warnings

No caffeine may be used while on this remedy.

Directions

Apply 1-2 pumps M-F only to the inner parts of forearm or upper arm on clean skin. Once symptoms recede, you may reduce usage.

Inactive Ingredients

Aloe vera leaf juice extract, Benzyl Alcohol, Tocopherol, Acrylates C10-30 Alkyl Acrylate crosspolymer, Disodium EDTA, Sodium hydroxide, water, ethylhexylglycerin , chelidonium majus whole